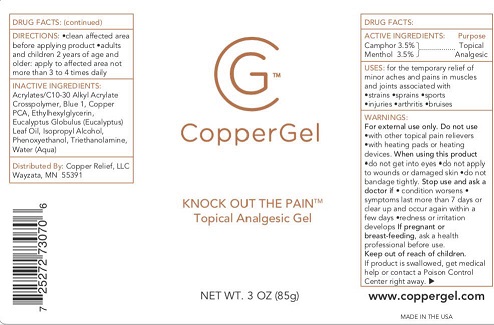 DRUG LABEL: CopperGel
NDC: 72081-001 | Form: GEL
Manufacturer: CopperRelief, LLC
Category: otc | Type: HUMAN OTC DRUG LABEL
Date: 20180204

ACTIVE INGREDIENTS: MENTHOL 3.5 g/100 g; CAMPHOR (SYNTHETIC) 3.5 g/100 g
INACTIVE INGREDIENTS: PHENOXYETHANOL; TROLAMINE; CARBOMER COPOLYMER TYPE A (ALLYL PENTAERYTHRITOL CROSSLINKED); EUCALYPTUS GLOBULUS LEAF; ISOPROPYL ALCOHOL; COPPER PIDOLATE; WATER; ETHYLHEXYLGLYCERIN; FD&C BLUE NO. 1

CopperGel

DRUG FACTS:

ACTIVE INGREDIENTS:

Camphor 3.5%

Menthol 3.5%

Purpose:

Topical Analgesic

INDICATIONS AND USAGE

USES: for the temporary relief of minor aches and pains in muscles and joints associated with:

- strains
- sprains
- sports injuries
- arthritis
- bruises

WARNINGS:

For external use only.

Do not use

- with other topical pain relievers
- with heating pads or heating devices

When using this product

- do not get into eyes
- do not apply to wounds or damaged skin
- do not bandage tightly

Stop use and ask a doctor if

- condition worsens
- symptoms last more than 7 days or clear up and occur again within a few days
- redness or irritation develops

PREGNANCY OR BREAST FEEDING

If pregnant or breast-feeding, ask a health professional before use.

Keep out of reach of children. If product is swallowed, get medical help or contact a Poison Control Center right away.

DIRECTIONS:

- clean the affected area before applying product
- adults and children 2 years of age and older: apply to affected not more than 3 to 4 times daily

INACTIVE INGREDIENT

INACTIVE INGREDIENTS: Acrylates/C10-30 Alkyl Acrylate Crosspolymer, Blue 1, Copper PCA, Ethylhexylglycerin, Eucalyptus Globulus (Eucalyptus) Leaf Oil, Isopropyl Alcohol, Phenoxyethanol, Triethanolamine, Water (Aqua)

Distributed By: Copper Relief, LLC

Wayzata, MN 55391

www.coppergel.com

MADE IN THE USA

PACKAGE LABEL

CopperGel

KNOCK OUT THE PAIN™
Topical Analgesic Gel

NET WT. 3 OZ (85g)